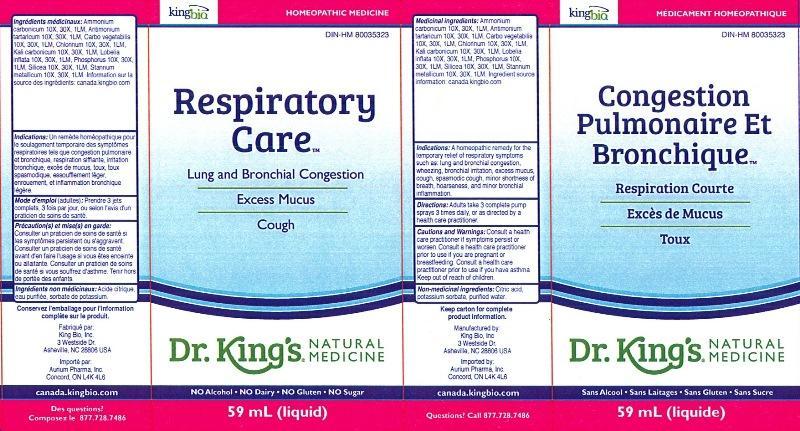 DRUG LABEL: Respiratory Care / Congestion Pulmonaire Et Bronchique
NDC: 57955-1806 | Form: LIQUID
Manufacturer: King Bio Inc.
Category: homeopathic | Type: HUMAN OTC DRUG LABEL
Date: 20140825

ACTIVE INGREDIENTS: AMMONIUM CARBONATE 10 [hp_X]/59 mL; ANTIMONY POTASSIUM TARTRATE 10 [hp_X]/59 mL; ACTIVATED CHARCOAL 10 [hp_X]/59 mL; CHLORINE 10 [hp_X]/59 mL; POTASSIUM CARBONATE 10 [hp_X]/59 mL; LOBELIA INFLATA 10 [hp_X]/59 mL; PHOSPHORUS 10 [hp_X]/59 mL; SILICON DIOXIDE 10 [hp_X]/59 mL; TIN 10 [hp_X]/59 mL
INACTIVE INGREDIENTS: CITRIC ACID MONOHYDRATE; POTASSIUM SORBATE; WATER

Respiratory Care Congestion Pulmonaire Et Bronchique

ACTIVE INGREDIENT

Medicinal ingredients/Ingrédients médicinaux: Ammonium carbonicum 10X, 30X, 1LM, Antimonium tartaricum 10X, 30X, 1LM, Carbo vegetabilis 10X, 30X, 1LM, Chlorinum 10X, 30X, 1LM, Kali carbonicum 10X, 30X, 1LM, Lobelia inflata 10X, 30X, 1LM, Phosphorus 10X, 30X, 1LM, Silicea 10X, 30X, 1LM, Stannum metallicum 10X, 30X, 1LM. Ingredient source information: canada.kingbio.com Information sur la source des ingrédients: canada.kingbio.com

INACTIVE INGREDIENT

Non-medicinal ingredients: Citric acid, Potassium sorbate, purified water.

Ingrédients non médicinaux: Acide citrique, eau purifiée, sorbate de potassium.

PURPOSE

Indications: A homeopathic remedy for the temporary relief of respiratory symptoms such as: lung and bronchial congestion, wheezing, bronchial irritation, excess mucus, cough, spasmodic cough, minor shortness of breath, hoarseness, and minor bronchial inflammation.

Indications: un remède homéopathique pour le soulagement temporaire des symptômes respiratoires tels que congestion pulmonaire et bronchique, respiration sifflante, irritation bronchique, excès de mucus, toux, toux spasmodique, essoufflement léger, enrouement, et inflammation bronchique léger, enrouement, et inflammation bronchique légère.

DOSAGE AND ADMINISTRATION

Directions: Adults take 3 complete pump sprays, 3 times daily, or as directed by a health care practitioner.

Mode d'emploi (adultes): Prendre 3 jets complets, 3 fois par jour, ou selon l'avis d'un praticien de soins de santé.

INDICATIONS AND USAGE

Indications: A homeopathic remedy for the temporary relief of respiratory symptoms such as:

- lung and bronchial congestion
- wheezing
- bronchial irritation
- excess mucus
- cough
- spasmodic cough
- minor shortness of breath
- hoarseness
- minor bronchial inflammation

Indications: un remède homéopathique pour le soulagement temporaire des symptômes respiratoires tels que congestion pulmonaire et bronchique, respiration sifflante, irritation bronchique, excès de mucus, toux, toux spasmodique, essoufflement léger, enrouement, et inflammation bronchique léger, enrouement, et inflammation bronchique légère.

WARNINGS

Cautions and Warnings: Consult a health care practitioner if symptoms persist or worsen. Consult a health care practitioner prior to use if you are pregnant or breastfeeding.

Précaution(s) et mise(s) en garde: Consulter un praticien de soins de santé si les symptômes persistent ou s'aggravent. Consulter un praticien de soins de santé avant d'en faire l'usage si vous êtes enceinte ou allaitante.

Keep out of reach of children.

Tenir hors de portée des enfants.